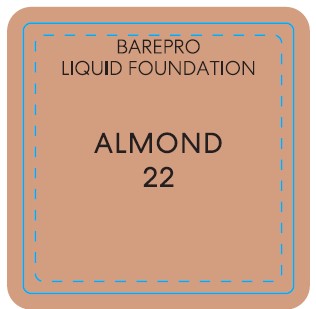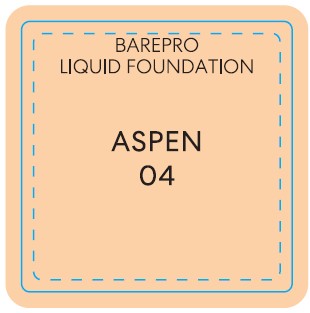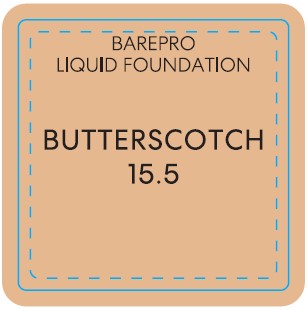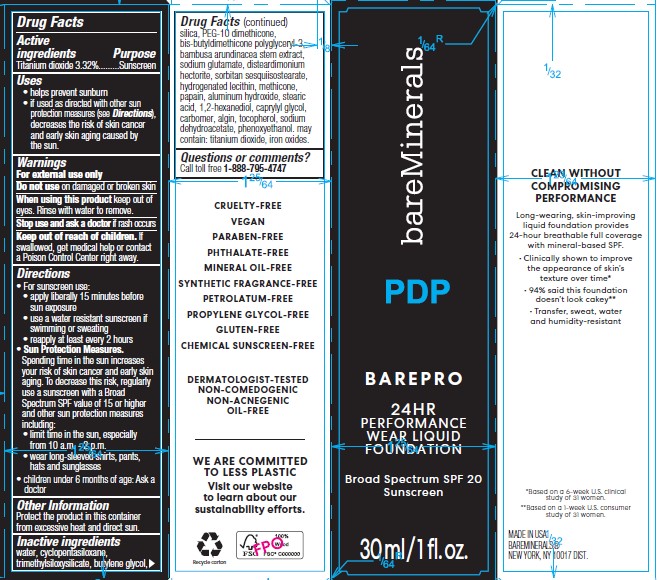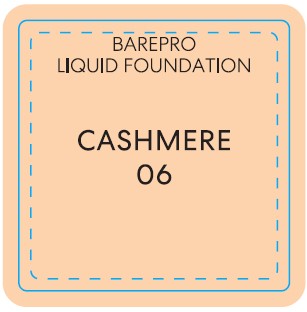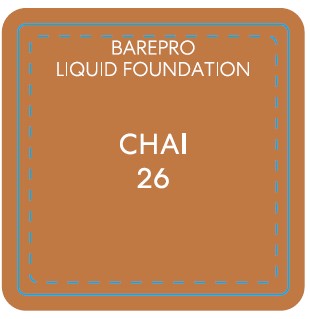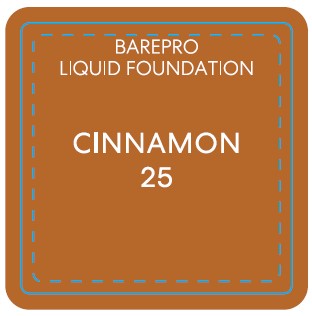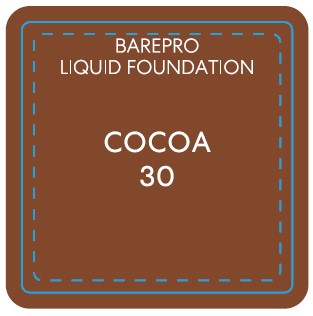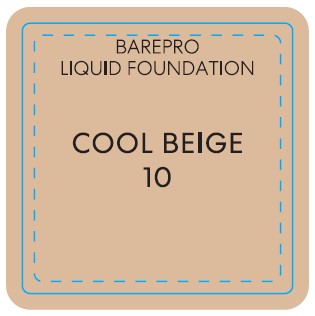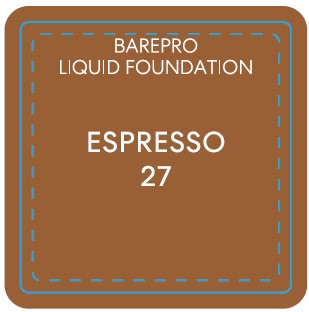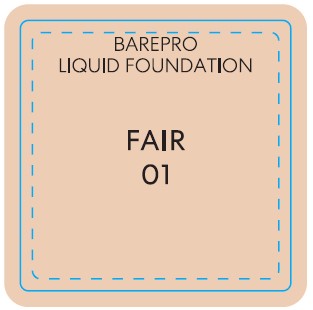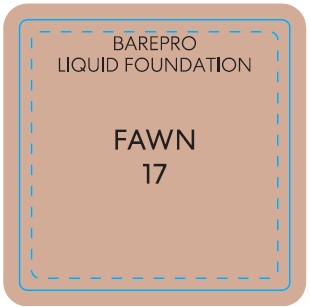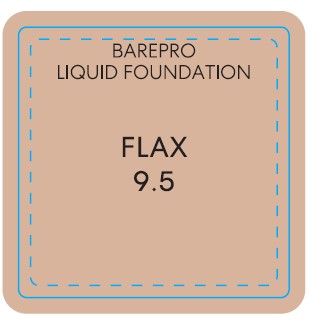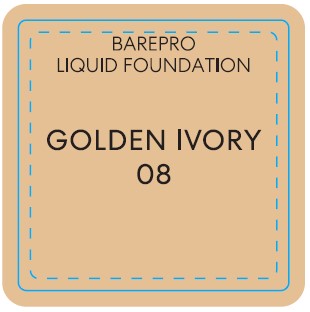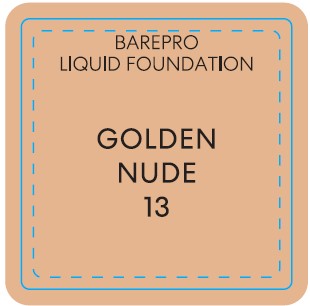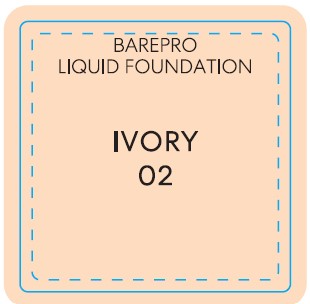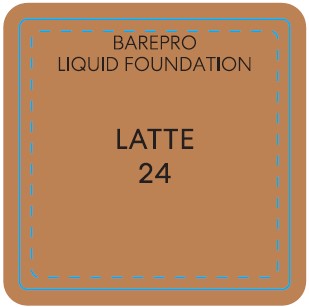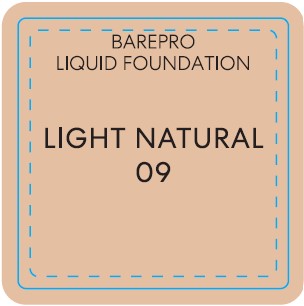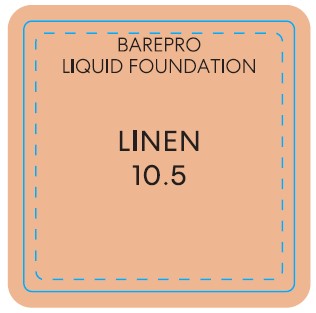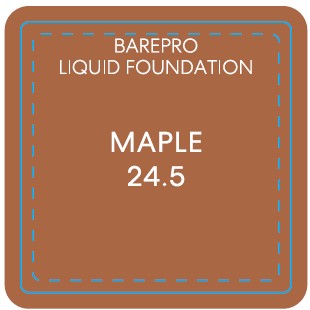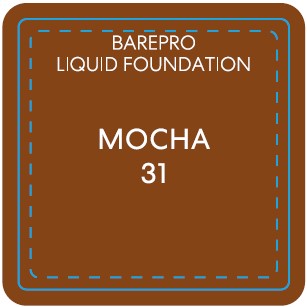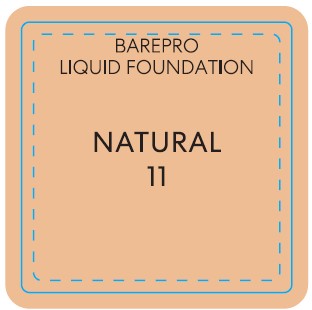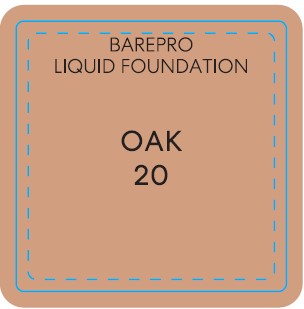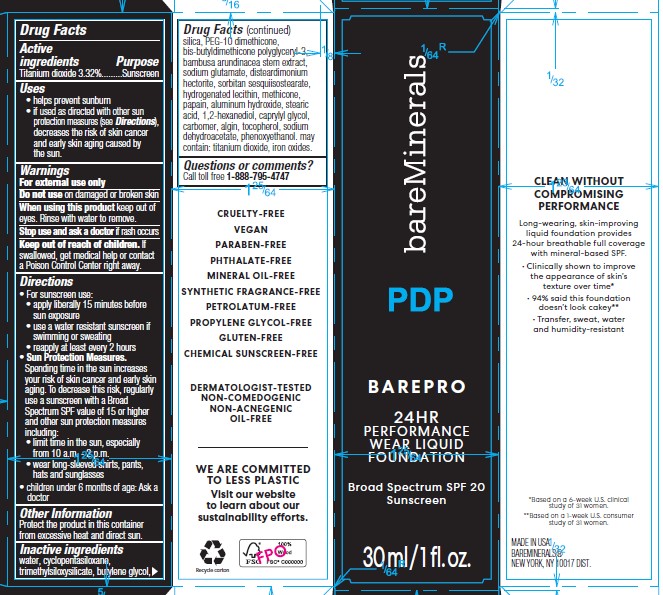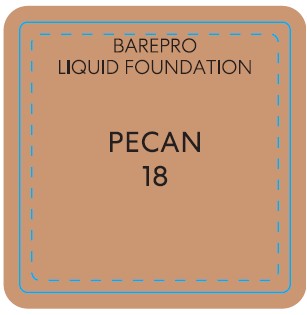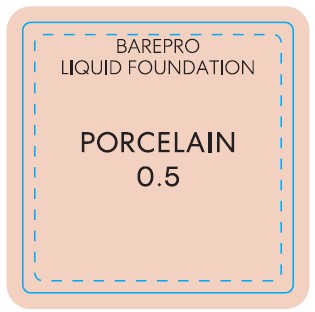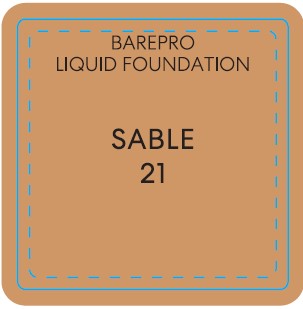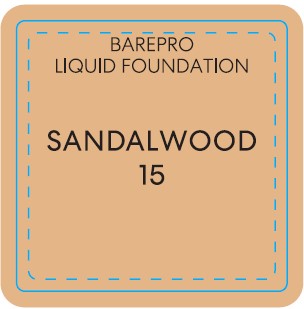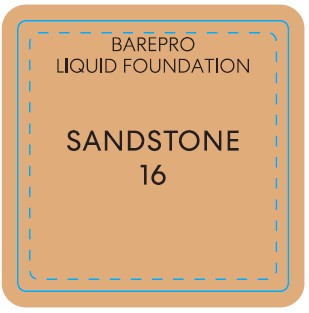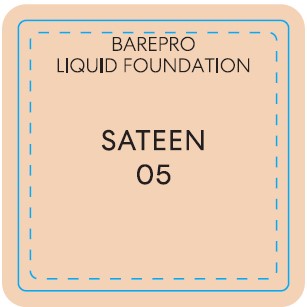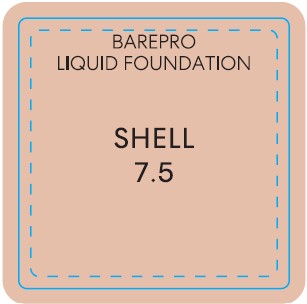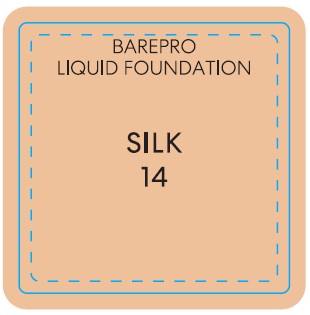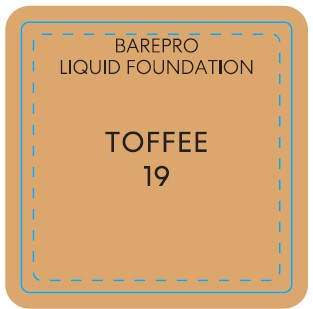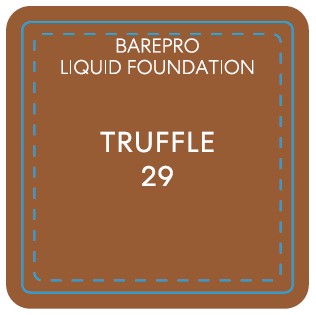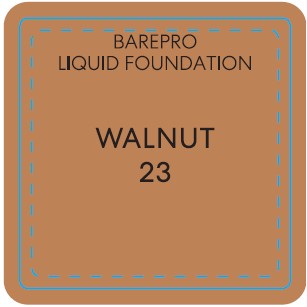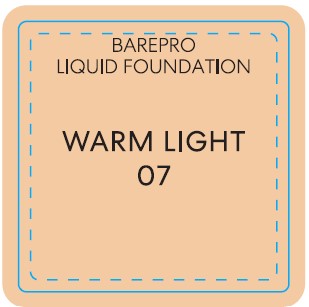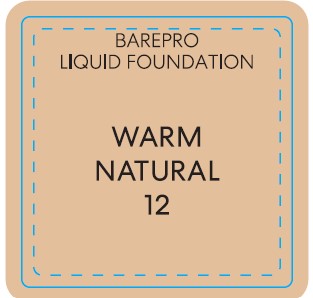 DRUG LABEL: bareMinerals BAREPRO Performance Wear Liquid Foundation Broad Spectrum SPF 20
NDC: 98132-310 | Form: LIQUID
Manufacturer: Orveon Global US LLC
Category: otc | Type: HUMAN OTC DRUG LABEL
Date: 20231213

ACTIVE INGREDIENTS: TITANIUM DIOXIDE 33.2 mg/1 mL
INACTIVE INGREDIENTS: WATER; CYCLOMETHICONE 5; TRIMETHYLSILOXYSILICATE (M/Q 0.8-1.0); BUTYLENE GLYCOL; SILICON DIOXIDE; PEG-10 DIMETHICONE (600 CST); BAMBUSA BAMBOS STEM; MONOSODIUM GLUTAMATE; DISTEARDIMONIUM HECTORITE; HYDROGENATED SOYBEAN LECITHIN; METHICONE (20 CST); PAPAIN; ALUMINUM HYDROXIDE; STEARIC ACID; 1,2-HEXANEDIOL; CAPRYLYL GLYCOL; CARBOXYPOLYMETHYLENE; SODIUM ALGINATE; TOCOPHEROL; SODIUM DEHYDROACETATE; PHENOXYETHANOL; FERRIC OXIDE RED

bareMinerals® BAREPRO™ Performance Wear Liquid Foundation Broad Spectrum SPF 20

Drug Facts

Active ingredient(s)

Titanium dioxide 3.32%

Purpose

Sunscreen

Uses

- helps prevent sunburn
- if used as directed with other sun protection measures (see Directions), decreases the risk of skin cancer and early skin aging caused by the sun

Warnings

For external use only

Do not use on damaged or broken skin

When using this product keep out of eyes. Rinse with water to remove.

Stop use and ask a doctor if rash occurs

Keep out of reach of children. If product is swallowed, get medical help or contact a Poison Control Center right away.

Directions

For sunscreen use:

- apply liberally 15 minutes before sun exposure
- use a water resistant sunscreen if swimming or sweating
- reapply at least every 2 hours
- children under 6 months: ask a doctor
- Sun protection measures. Spending time in the sun increases your risk of skin cancer and early skin aging. To decrease this risk, regularly use a sunscreen with a Broad Spectrum SPF of 15 or higher and other sun protection measures including:
  - limit time in the sun, especially from 10 a.m. – 2 p.m.
  - wear long-sleeve shirts, pants, hats, and sunglasses

Inactive ingredients

water, cyclopentasiloxane, trimethylsiloxysilicate, butylene glycol, silica, peg-10 dimethicone, bis-butyldimethicone polyglyceryl-3, bambusa arundinacea stem extract, sodium glutamate, disteardimonium hectorite, sorbitan sesquiisostearate, hydrogenated lecithin, methicone, papain, aluminum hydroxide, stearic acid, 1,2-hexanediol, caprylyl glycol, carbomer, algin, tocopherol, sodium dehydroacetate, phenoxyethanol.

may contain (+/-): titanium dioxide, iron oxides.

Other information

Protect this product from excessive heat and direct sun

Questions or comments?

Call toll free 1-888-795-4747

Dist. by Bare Escentuals Beauty, Inc., SF, CA 94105 USA • London W1F 8ZU

PRINCIPAL DISPLAY PANEL - 30 ml Bottle Carton - Fair 01

bareMinerals®

BARE PRO™

PERFORMANCE WEAR
LIQUID FOUNDATION
BROAD SPECTRUM SPF 20

30 ml / 1 fl. oz.

PRINCIPAL DISPLAY PANEL - 30 ml Bottle Carton - Porcelain 0.5

bareMinerals®

BARE PRO™

PERFORMANCE WEAR
LIQUID FOUNDATION
BROAD SPECTRUM SPF 20

30 ml / 1 fl. oz.

PRINCIPAL DISPLAY PANEL - 30 ml Bottle Carton - Ivory 02

bareMinerals®

BARE PRO™

PERFORMANCE WEAR
LIQUID FOUNDATION
BROAD SPECTRUM SPF 20

30 ml / 1 fl. oz.

PRINCIPAL DISPLAY PANEL - 30 ml Bottle Carton - Aspen 04

bareMinerals®

BARE PRO™

PERFORMANCE WEAR
LIQUID FOUNDATION
BROAD SPECTRUM SPF 20

30 ml / 1 fl. oz.

PRINCIPAL DISPLAY PANEL - 30 ml Bottle Carton - Sateen 05

bareMinerals®

BARE PRO™

PERFORMANCE WEAR
LIQUID FOUNDATION
BROAD SPECTRUM SPF 20

30 ml / 1 fl. oz.

PRINCIPAL DISPLAY PANEL - 30 ml Bottle Carton - Cashmere 06

bareMinerals®

BARE PRO™

PERFORMANCE WEAR
LIQUID FOUNDATION
BROAD SPECTRUM SPF 20

30 ml / 1 fl. oz.

PRINCIPAL DISPLAY PANEL - 30 ml Bottle Carton - Warm Light 07

bareMinerals®

BARE PRO™

PERFORMANCE WEAR
LIQUID FOUNDATION
BROAD SPECTRUM SPF 20

30 ml / 1 fl. oz.

PRINCIPAL DISPLAY PANEL - 30 ml Bottle Carton - Golden Ivory 08

bareMinerals®

BARE PRO™

PERFORMANCE WEAR
LIQUID FOUNDATION
BROAD SPECTRUM SPF 20

30 ml / 1 fl. oz.

PRINCIPAL DISPLAY PANEL - 30 ml Bottle Carton - Shell 7.5

bareMinerals®

BARE PRO™

PERFORMANCE WEAR
LIQUID FOUNDATION
BROAD SPECTRUM SPF 20

30 ml / 1 fl. oz.

PRINCIPAL DISPLAY PANEL - 30 ml Bottle Carton - Cool Beige 10

bareMinerals®

BARE PRO™

PERFORMANCE WEAR
LIQUID FOUNDATION
BROAD SPECTRUM SPF 20

30 ml / 1 fl. oz.

PRINCIPAL DISPLAY PANEL - 30 ml Bottle Carton - Flax 9.5

bareMinerals®

BARE PRO™

PERFORMANCE WEAR
LIQUID FOUNDATION
BROAD SPECTRUM SPF 20

30 ml / 1 fl. oz.

PRINCIPAL DISPLAY PANEL - 30 ml Bottle Carton - Linen 10.5

bareMinerals®

BARE PRO™

PERFORMANCE WEAR
LIQUID FOUNDATION
BROAD SPECTRUM SPF 20

30 ml / 1 fl. oz.

PRINCIPAL DISPLAY PANEL - 30 ml Bottle Carton - Golden Nude 13

bareMinerals®

BARE PRO™

PERFORMANCE WEAR
LIQUID FOUNDATION
BROAD SPECTRUM SPF 20

30 ml / 1 fl. oz.

PRINCIPAL DISPLAY PANEL - 30 ml Bottle Carton - Silk 14

bareMinerals®

BARE PRO™

PERFORMANCE WEAR
LIQUID FOUNDATION
BROAD SPECTRUM SPF 20

30 ml / 1 fl. oz.

PRINCIPAL DISPLAY PANEL - 30 ml Bottle Carton - Butterscotch 15.5

bareMinerals®

BARE PRO™

PERFORMANCE WEAR
LIQUID FOUNDATION
BROAD SPECTRUM SPF 20

30 ml / 1 fl. oz

PRINCIPAL DISPLAY PANEL - 30 ml Bottle Carton - Sandstone 16

bareMinerals®

BARE PRO™

PERFORMANCE WEAR
LIQUID FOUNDATION
BROAD SPECTRUM SPF 20

30 ml / 1 fl. oz.

PRINCIPAL DISPLAY PANEL - 30 ml Bottle Carton - Fawn 17

bareMinerals®

BARE PRO™

PERFORMANCE WEAR
LIQUID FOUNDATION
BROAD SPECTRUM SPF 20

30 ml / 1 fl. oz.

PRINCIPAL DISPLAY PANEL - 30 ml Bottle Carton - Pecan 18

bareMinerals®

BARE PRO™

PERFORMANCE WEAR
LIQUID FOUNDATION
BROAD SPECTRUM SPF 20

30 ml / 1 fl. oz.

PRINCIPAL DISPLAY PANEL - 30 ml Bottle Carton - Toffee 19

bareMinerals®

BARE PRO™

PERFORMANCE WEAR
LIQUID FOUNDATION
BROAD SPECTRUM SPF 20

30 ml / 1 fl. oz.

PRINCIPAL DISPLAY PANEL - 30 ml Bottle Carton - Oak 20

bareMinerals®

BARE PRO™

PERFORMANCE WEAR
LIQUID FOUNDATION
BROAD SPECTRUM SPF 20

30 ml / 1 fl. oz.

PRINCIPAL DISPLAY PANEL - 30 ml Bottle Carton - Sable 21

bareMinerals®

BARE PRO™

PERFORMANCE WEAR
LIQUID FOUNDATION
BROAD SPECTRUM SPF 20

30 ml / 1 fl. oz.

PRINCIPAL DISPLAY PANEL - 30 ml Bottle Carton - Almond 22

bareMinerals®

BARE PRO™

PERFORMANCE WEAR
LIQUID FOUNDATION
BROAD SPECTRUM SPF 20

30 ml / 1 fl. oz.

PRINCIPAL DISPLAY PANEL - 30 ml Bottle Carton - Walnut 23

bareMinerals®

BARE PRO™

PERFORMANCE WEAR
LIQUID FOUNDATION
BROAD SPECTRUM SPF 20

30 ml / 1 fl. oz.

PRINCIPAL DISPLAY PANEL - 30 ml Bottle Carton - Latte 24

bareMinerals®

BARE PRO™

PERFORMANCE WEAR
LIQUID FOUNDATION
BROAD SPECTRUM SPF 20

30 ml / 1 fl. oz.

PRINCIPAL DISPLAY PANEL - 30 ml Bottle Carton - Cinnamon 25

bareMinerals®

BARE PRO™

PERFORMANCE WEAR
LIQUID FOUNDATION
BROAD SPECTRUM SPF 20

30 ml / 1 fl. oz.

PRINCIPAL DISPLAY PANEL - 30 ml Bottle Carton - Chai 26

bareMinerals®

BARE PRO™

PERFORMANCE WEAR
LIQUID FOUNDATION
BROAD SPECTRUM SPF 20

30 ml / 1 fl. oz.

PRINCIPAL DISPLAY PANEL - 30 ml Bottle Carton - Espresso 27

bareMinerals®

BARE PRO™

PERFORMANCE WEAR
LIQUID FOUNDATION
BROAD SPECTRUM SPF 20

30 ml / 1 fl. oz

PRINCIPAL DISPLAY PANEL - 30 ml Bottle Carton - Mocha 31

bareMinerals®

BARE PRO™

PERFORMANCE WEAR
LIQUID FOUNDATION
BROAD SPECTRUM SPF 20

30 ml / 1 fl. oz.

PRINCIPAL DISPLAY PANEL - 30 ml Bottle Carton - Truffle 29

bareMinerals®

BARE PRO™

PERFORMANCE WEAR
LIQUID FOUNDATION
BROAD SPECTRUM SPF 20

30 ml / 1 fl. oz

PRINCIPAL DISPLAY PANEL - 30 ml Bottle Carton - Cocoa 30

bareMinerals®

BARE PRO™

PERFORMANCE WEAR
LIQUID FOUNDATION
BROAD SPECTRUM SPF 20

30 ml / 1 fl. oz.

PRINCIPAL DISPLAY PANEL - 30 ml Bottle Carton - Maple 24.5

bareMinerals ®
BARE PRO™
PERFORMANCE WEAR
LIQUID FOUNDATION
BROAD SPECTRUM SPF 20
30 ml / 1 fl. oz.

PRINCIPAL DISPLAY PANEL - 30 ml Bottle Carton - Light Natural 09

bareMinerals ®

BARE PRO™

PERFORMANCE WEAR
LIQUID FOUNDATION
BROAD SPECTRUM SPF 20

30 ml / 1 fl. oz.

PRINCIPAL DISPLAY PANEL - 30 ml Bottle Carton - Natural 11

bareMinerals ®

BARE PRO™

PERFORMANCE WEAR
LIQUID FOUNDATION
BROAD SPECTRUM SPF 20

30 ml / 1 fl. oz.

PRINCIPAL DISPLAY PANEL - 30 ml Bottle Carton - Sandalwood 15

bareMinerals ®

BARE PRO™

PERFORMANCE WEAR
LIQUID FOUNDATION
BROAD SPECTRUM SPF 20

30 ml / 1 fl. oz.

PRINCIPAL DISPLAY PANEL - 30 ml Bottle Carton - Warm Natural 12

bareMinerals ®

BARE PRO™

PERFORMANCE WEAR
LIQUID FOUNDATION
BROAD SPECTRUM SPF 20

30 ml / 1 fl. oz.

PRINCIPAL DISPLAY PANEL - 30 ml Bottle Carton - Camel 17

Camel 17